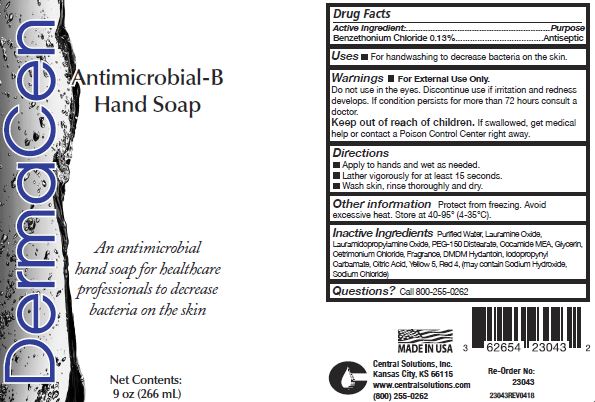 DRUG LABEL: DermaCen Antimicrobial-B Hand
NDC: 62654-232 | Form: SOLUTION
Manufacturer: Central Solutions Inc
Category: otc | Type: HUMAN OTC DRUG LABEL
Date: 20241209

ACTIVE INGREDIENTS: BENZETHONIUM CHLORIDE 0.13 g/100 mL
INACTIVE INGREDIENTS: WATER; LAURAMINE OXIDE; LAURAMIDOPROPYLAMINE OXIDE; PEG-150 DISTEARATE; COCO MONOETHANOLAMIDE; GLYCERIN; CETRIMONIUM CHLORIDE; DMDM HYDANTOIN; IODOPROPYNYL BUTYLCARBAMATE; CITRIC ACID MONOHYDRATE; FD&C YELLOW NO. 5; FD&C RED NO. 4; SODIUM HYDROXIDE; SODIUM CHLORIDE

Drug Facts 62654-232

Active ingredient:

Benzethonium Chloride 0.13%

Purpose

Antiseptic

Uses

For handwashing to decrease bacteria on the skin.

Warnings

For External Use Only.

Do not use in the eyes.

Discontinue use if irritation and redness develops.

If condition persists for more than 72 hours consult a doctor.

Keep out of reach of children.

If swallowed, get medical help or contact a Poison Control Center right away.

Directions

Apply to hands and wet as needed.

Lather vigorously for at least 15 seconds.

Wash skin, rinse thoroughly and dry.

Other information

Protect from freezing.Avoid excessive heat.

Store at 40-95 F (4-35 C)

Inactive Ingredients

Purified Water, Lauramine Oxide,Lauramidopropylamine Oxide, PEG-150 Distearate, Cocamide MEA, Glycerin, Cetrimonium Chloride, Fragrance, DMDM Hydantoin, Iodopropynyl Carbamate, Citric Acid, Yellow 5, Red 4, (may contain Sodium Hydroxide, Sodium Chloride).

Questions?

Call 800-255-0262

PACKAGE LABEL

DermaCen

Antimicrobial-B

Hand Soap

An antimicrobial

hand soap for healthcare

professionals to decrease

bacteria on the skin

Net Contents:

9 oz (266mL)